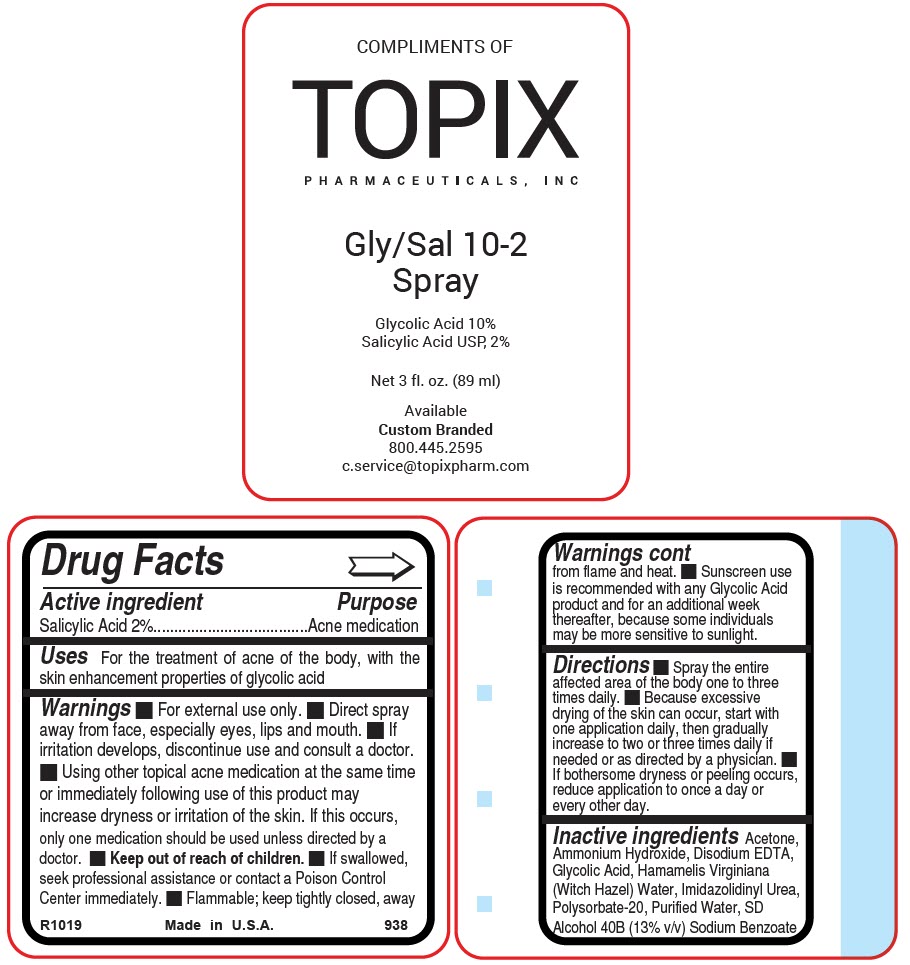 DRUG LABEL: Gly-Sal 10-2
NDC: 51326-938 | Form: LIQUID
Manufacturer: Topiderm, Inc.
Category: otc | Type: HUMAN OTC DRUG LABEL
Date: 20240613

ACTIVE INGREDIENTS: SALICYLIC ACID 20 mg/1 mL
INACTIVE INGREDIENTS: GLYCOLIC ACID 100 mg/1 mL; GREEN TEA LEAF; COCAMIDOPROPYL BETAINE; EDETATE DISODIUM; LINOLEAMIDOPROPYL PROPYLENE GLYCOL-DIMONIUM CHLORIDE PHOSPHATE; POLYSORBATE 20; WATER; FD&C RED NO. 40; SODIUM C12-15 ALKETH-15 SULFONATE; SODIUM C14-16 OLEFIN SULFONATE; TROLAMINE; FD&C YELLOW NO. 5; ZINC PIDOLATE

Gly-Sal 10-2
Spray

Drug Facts

Active ingredient

Salicylic Acid 2%

Purpose

Acne medication

Uses

For the treatment of acne of the body, with the skin enhancement properties of glycolic acid

Warnings

- For external use only.
- Direct spray away from face, especially eyes, lips and mouth.
- If irritation develops, discontinue use and consult a doctor.
- Using other topical acne medication at the same time or immediately following use of this product may increase dryness or irritation of the skin. If this occurs, only one medication should be used unless directed by a doctor.

- Keep out of reach of children.
- If swallowed, seek professional assistance or contact a Poison Control Center immediately.
- Flammable; keep tightly closed, away from flame and heat.
- Sunscreen use is recommended with any Glycolic Acid product and for an additional week thereafter, because some individuals may be more sensitive to sunlight.

Directions

- Spray the entire affected area of the body one to three times daily.
- Because excessive drying of the skin can occur, start with one application daily, then gradually increase to two or three times daily if needed or as directed by a physician.
- If bothersome dryness or peeling occurs, reduce application to once a day or every other day.

Inactive ingredients

Acetone, Ammonium Hydroxide, Disodium EDTA, Glycolic Acid, Hamamelis Virginiana (Witch Hazel) Water, Imidazolidinyl Urea, Polysorbate-20, Purified Water, SD Alcohol 40B (13% v/v) Sodium Benzoate

PRINCIPAL DISPLAY PANEL - 89 ml Bottle Label

COMPLIMENTS OF

TOPIX
PHARMACEUTICALS, INC

Gly/Sal 10-2
Spray

Glycolic Acid 10%
Salicylic Acid USP, 2%

Net 3 fl. oz. (89 ml)

Available
Custom Branded
800.445.2595
c.service@topixpharm.com